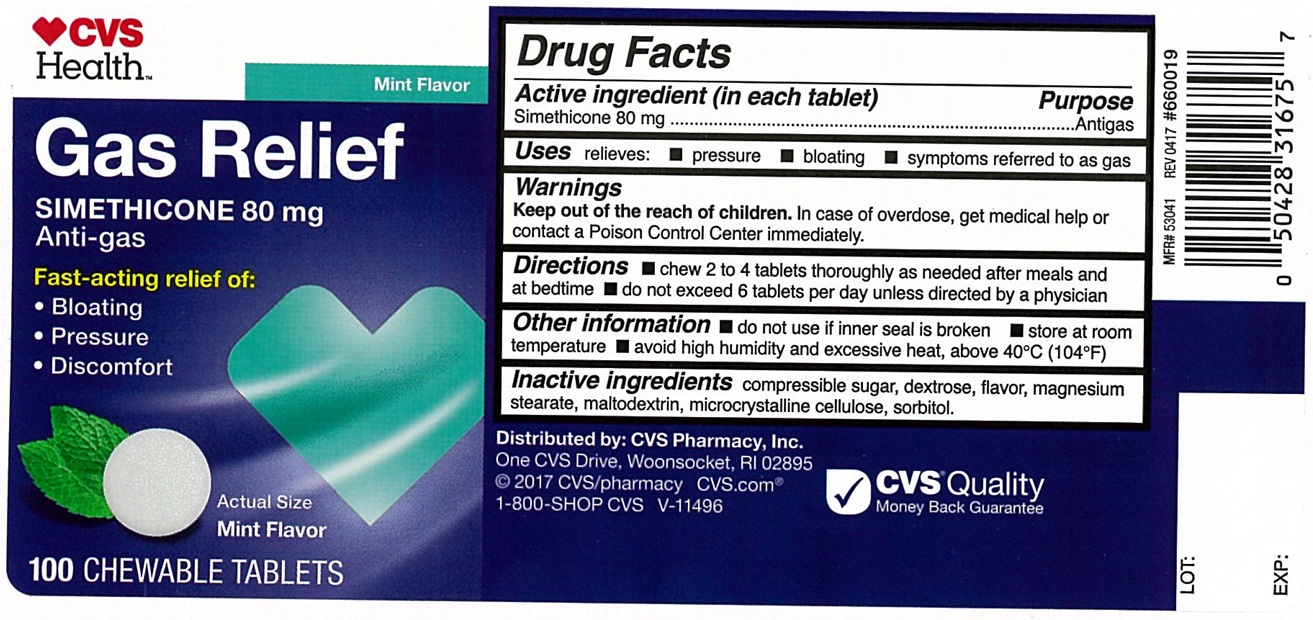 DRUG LABEL: Gas relief Anti-gas
NDC: 51316-904 | Form: TABLET, CHEWABLE
Manufacturer: CVS
Category: otc | Type: Human OTC Drug Label
Date: 20250129

ACTIVE INGREDIENTS: DIMETHICONE 80 mg/1 1
INACTIVE INGREDIENTS: SUGARCANE; MALTODEXTRIN; DEXTROSE, UNSPECIFIED FORM; MAGNESIUM STEARATE; MICROCRYSTALLINE CELLULOSE; SORBITOL

Gas Relief Anti-gas Chewable Tablets

ACTIVE INGREDIENT(in each tablet)

Simethicone 80 mg

PURPOSE

Antigas

USE(S)

relieves:

- pressure
- bloating
- symptoms referred to as gas

WARNINGS

.

KEEP OUT OF REACH OF CHILDREN

In case of overdose, get medical help or contact a Poison Control Center immediately.

DIRECTIONS

- chew 2 to 4 tablets thoroughly as needed after meals and at bedtime
- do not exceed 6 tablets per day unless directed by a physician

OTHER INFORMATION

- do not use if inner seal is broken
- store at room temperature
- avoid high humidity and excessive heat, above 40oC (104oF)

INACTIVE INGREDIENTS

compressible sugar, dextrose, flavor, magnesium stearate, maltodextrin, microcrystalline cellulose, sorbitol.

PRINCIPAL DISPLAY PANEL

CVS Health™

Mint Flavor

NDC 51316-904-16

Gas Relief
SIMETHICONE 80 mg
Anti-gas
Fast-acting relief of:

- Pressure
- Bloating
- Discomfort

Mint Flavor
100 CHEWABLE TABLETS